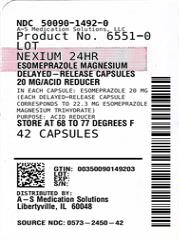 DRUG LABEL: Nexium 24HR
NDC: 50090-1492 | Form: CAPSULE, DELAYED RELEASE
Manufacturer: A-S Medication Solutions
Category: otc | Type: HUMAN OTC DRUG LABEL
Date: 20240514

ACTIVE INGREDIENTS: ESOMEPRAZOLE MAGNESIUM 20 mg/1 1
INACTIVE INGREDIENTS: STARCH, CORN; D&C RED NO. 28; FD&C BLUE NO. 1; FD&C RED NO. 40; FERRIC OXIDE RED; GELATIN, UNSPECIFIED; GLYCERYL MONOSTEARATE; HYDROXYPROPYL CELLULOSE (1600000 WAMW); HYPROMELLOSE, UNSPECIFIED; MAGNESIUM STEARATE; METHACRYLIC ACID - METHYL METHACRYLATE COPOLYMER (1:1); POLYSORBATE 80; SUCROSE; TALC; TITANIUM DIOXIDE; TRIETHYL CITRATE

Drug Facts

Active ingredient (in each capsule)

Esomeprazole 20 mg

(Each delayed-release capsule corresponds to 22.3 mg

esomeprazole magnesium trihydrate)

Purpose

Acid reducer

Uses

- treats frequent heartburn (occurs 2 or moredays a week)
- not intended for immediate relief of heartburn; this drug may take 1 to 4 days for full effect

Warnings

Allergy alert:

- Do not use if you are allergic to esomeprazole
- Esomeprazole may cause severe skin reactions. Symptoms include:
- skin reddening
- blisters
- rash

If an allergic reaction occurs, stop use and seek medical attention right away.

Do not use if you have

- trouble or pain swallowing food, vomiting with blood, or bloody or black stools
- heartburn with lightheadedness, sweating or dizziness
- chest pain or shoulder pain with shortness of breath; sweating; pain spreading to arms, neck or shoulders; or lightheadedness
- frequent chest pain

These may be signs of a serious condition. See your doctor.

Ask a doctor before use if you have

- had heartburn over 3 months. This may be a sign of a more serious condition.
- frequent wheezing, particularly with heartburn
- unexplained weight loss
- nausea or vomiting
- stomach pain

ASK DOCTOR/PHARMACIST

1. Ask a doctor or pharmacist before use if you are
2. taking a prescription drug. Acid reducers may interact with certain prescription drugs.

Stop use and ask a doctor if

- your heartburn continues or worsens
- you need to take this product for more than 14 days
- you need to take more than 1 course of treatment every 4 months
- you get diarrhea
- you develop a rash or joint pain

PREGNANCY OR BREAST FEEDING

If pregnant or breast-feeding,ask a health professional before use.

Keep out of reach of children.In case of overdose, get medical help or contact a Poison Control Center right away.

Directions

- adults 18 years of age and older
- this product is to be used once a day (every 24 hours), every day for 14 days
- may take 1 to 4 days for full effect
  14-Day Course of Treatment Repeated 14-Day Courses (if needed)
  - swallow 1 capsule with a glass of water before eating in the morning
  - take every day for 14 days
  - do not take more than 1 capsule a day
  - swallow whole. Do not crush or chew capsules.
  - do not use for more than 14 days unless directed by your doctor
  - you may repeat a 14-day course every 4 months
  - do not take for more than 14 days or more often than every 4 months unless directed by a doctor
- children under 18 years of age: ask a doctor before use. Heartburn in children may sometimes be caused by a serious condition.

Other Information

- read the directions and warnings before use
- keep the carton. It contains important information.
- store at 20-25°C (68-77°F)

Inactive Ingredients (Nexium 24HR Capsules)

corn starch, D&C red no. 28, FD&C blue no. 1, FD&C red no. 40, ferric oxide, gelatin, glyceryl monostearate, hydroxypropyl cellulose, hypromellose, magnesium stearate, methacrylic acid copolymer, pharmaceutical ink, polysorbate 80, sucrose, talc, titanium dioxide, triethyl citrate

Inactive Ingredients (Nexium 24HR ClearMinis)

carmine, corn starch, FD&C blue no. 2, FD&C blue no. 2 aluminum lake, FD&C red no. 3, FD&C red no. 40, ferric oxide, gelatin, glyceryl monostearate, hydroxypropyl cellulose, hypromellose, magnesium stearate, methacrylic acid copolymer, pharmaceutical ink, polysorbate 80, sucrose, talc, titanium dioxide, triethyl citrate

Questions or comments?

call toll-free weekdays 9 AM to 5 PM EST at 1-866-226-1600

Additional Information

KEEP CARTON FOR COMPLETE WARNINGS AND IMPORTANT INFORMATION.

Do Not Use if seal under bottle cap imprinted with “SEALED for YOUR PROTECTION”

or yellow band around the center of each capsule is broken or missing.

Tips for Managing Heartburn

- Avoid foods or drinks that are more likely to cause heartburn, such as rich, spicy, fatty and fried foods, chocolate, caffeine, alcohol and even some acidic fruits and vegetables.
- Eat slowly and do not eat big meals.
- Do not eat late at night or just before bedtime.
- Do not lie flat or bend over soon after eating.
- Raise the head of your bed.
- Wear loose-fitting clothing around your stomach.
- If you are overweight, lose weight.
- If you smoke, quit smoking.

Distributed by: GSK Consumer Healthcare,

Warren, NJ 07059

©2022 GSK group of companies or its licensor

Made in France

For most recent product information, visit www.Nexium24HR.com

Nexium is a registered trademark of AstraZeneca AB and is used under license.

HOW SUPPLIED

Product: 50090-1492

NDC: 50090-1492-0 14 CAPSULE, DELAYED RELEASE in a BOTTLE / 3 in a CARTON